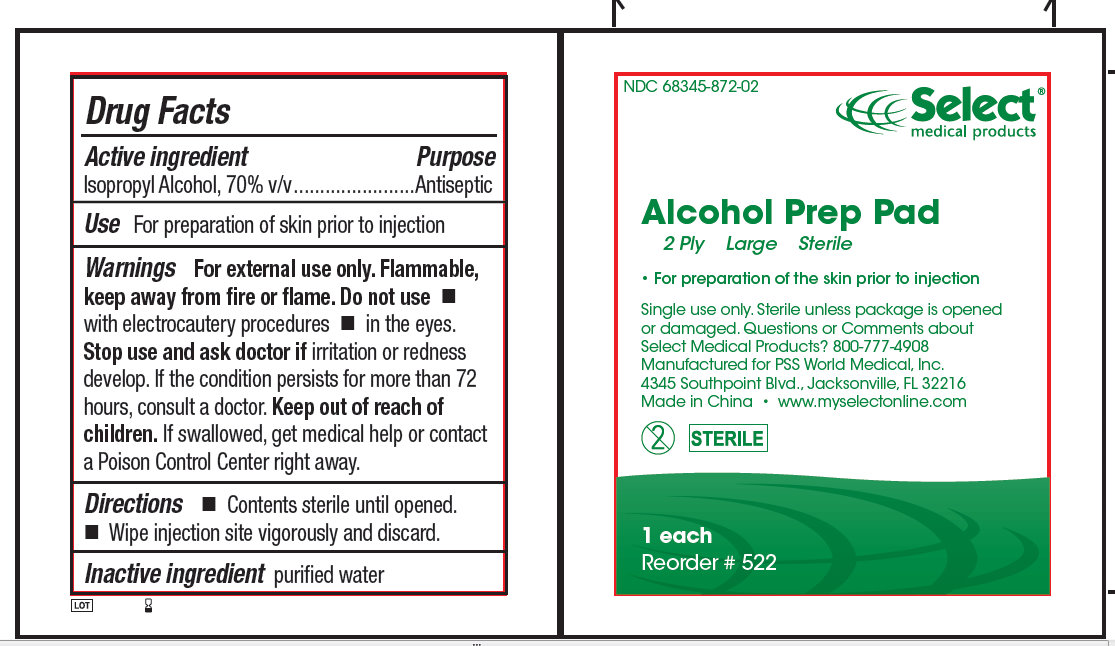 DRUG LABEL: Alcohol Prep Pads - Sterile
NDC: 68345-872 | Form: LIQUID
Manufacturer: PSS World Medical
Category: otc | Type: HUMAN OTC DRUG LABEL
Date: 20100603

ACTIVE INGREDIENTS: ISOPROPYL ALCOHOL 70 g/100 g
INACTIVE INGREDIENTS: WATER

Alcohol Prep Pads - Sterile

Active ingredient Purpose

Isopropyl Alcohol, 70 % v/v.................Antiseptic

PURPOSE

Use For preparation of the skin prior to an injection

Warnings

For external use only.

Flammable, keep away from fire or flame.

Do not use

- with electrocautery procedures
- in the eyes

Stop use and ask a doctor If irritation and redness develop. If condition persists for more than 72 hours, consult a doctor.

Keep out of reach of children. If swallowed, get medical help or contact a Poison Control Center right away.

Directions

- Contents sterile until opened.
- Wipe injection site vigorously and discard.

Inactive ingredient Purified water

Other information

Store at room temperature: 15 degree - 30 degree centigrade (59 degree - 86 degree F)

Questions or Comments about Select Medical Products? 800-777-4908

DESCRIPTION

Manufactured for PSS World Medical, Inc.

4345 Southpoint Blvd., Jacksonville, FL 32216

Made in China www.myselectonline.com

PACKAGE LABEL

Select medical products

Alcohol Prep Pads

2 Ply Large Sterile

For preparation of the skin prior to Injection
Single use only. Sterile unless package is opened or damaged.
2 STERILE
200 each/box
Reorder # 522
NDC 68345-872-02 Select medical products
Alcohol Prep Pads
2 Ply Large Sterile
For preparation of the skin prior to Injection
Single use only. Sterile unless package is opened or damaged.
2 STERILE
200 each/box
Reorder # 522
Select medical products
Alcohol Prep Pads
2 Ply Large Sterile
For preparation of the skin prior to Injection
Single use only. Sterile unless package is opened or damaged. Questions or Comments about select Medical Products? 800-777-4908
Manufactured for PSS World Medical, Inc.
4345 Southpoint Blvd., Jacksonville, FL 32216
Made in China www.myselectonline.com
2 STERILE
200 each/box
Reorder # 522
NDC 68345-872-02 Select medical products
Alcohol Prep Pads
2 Ply Large Sterile
For preparation of the skin prior to Injection
Single use only. Sterile unless package is opened or damaged.
2 STERILE LOT
200 each/box
Reorder # 522